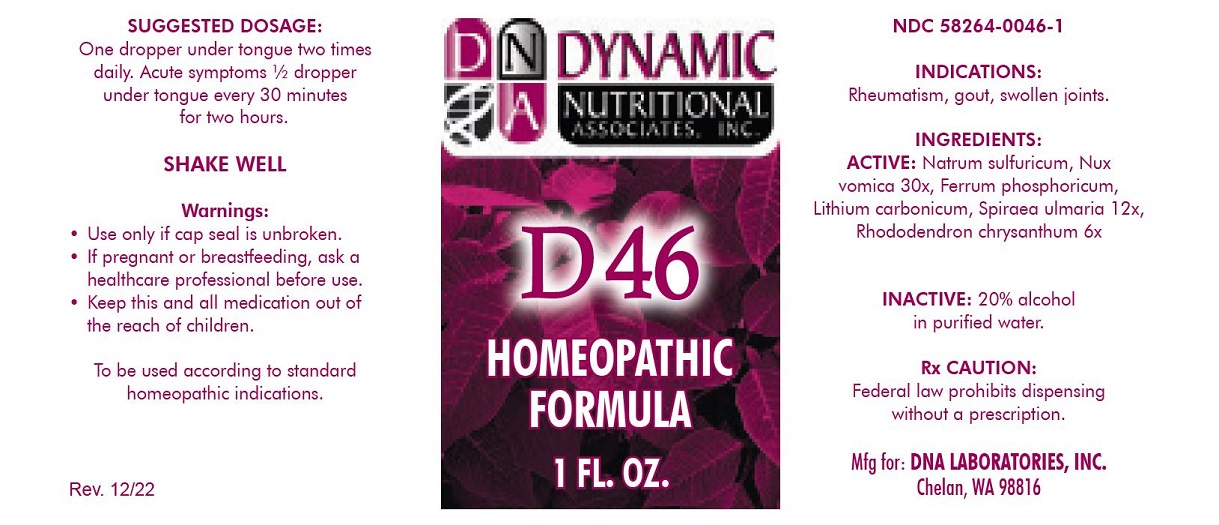 DRUG LABEL: D-46
NDC: 58264-0046 | Form: SOLUTION
Manufacturer: DNA Labs, Inc.
Category: homeopathic | Type: HUMAN OTC DRUG LABEL
Date: 20250113

ACTIVE INGREDIENTS: FERROSOFERRIC PHOSPHATE 12 [hp_X]/1 mL; LITHIUM CARBONATE 12 [hp_X]/1 mL; SODIUM SULFATE 30 [hp_X]/1 mL; STRYCHNOS NUX-VOMICA SEED 30 [hp_X]/1 mL; RHODODENDRON AUREUM LEAF 6 [hp_X]/1 mL; FILIPENDULA ULMARIA ROOT 12 [hp_X]/1 mL
INACTIVE INGREDIENTS: ALCOHOL; WATER

D-46

NDC 58264-0046-1

INDICATIONS

PURPOSE

Rheumatism, gout, swollen joints.

INGREDIENTS

ACTIVE

Ferrum phosphoricum 12x, Lithium carbonicum 12x, Natrum sulfuricum 30x, Nux vomica 30x, Rhododendron chrysanthum 6x, Spiraea ulmaria 12x

INACTIVE

20% alcohol in purified water.

Rx CAUTION

Federal law prohibits dispensing without a prescription.

SUGGESTED DOSAGE

One dropper under tongue two times daily. Acute symptoms ½ dropper under tongue every 30 minutes for two hours.

STORAGE AND HANDLING

SHAKE WELL

Warnings

- Use only if cap seal is unbroken.

PREGNANCY OR BREAST FEEDING

- If pregnant or breastfeeding, ask a healthcare professional before use.

KEEP OUT OF REACH OF CHILDREN

- Keep this and all medication out of the reach of children.

To be used according to standard homeopathic indications.

PRINCIPAL DISPLAY PANEL - 1 FL. OZ. Bottle Label

DYNAMIC

NUTRITIONAL

ASSOCIATES, INC.

D 46

HOMEOPATHIC

STRESS FORMULA

1 FL. OZ.